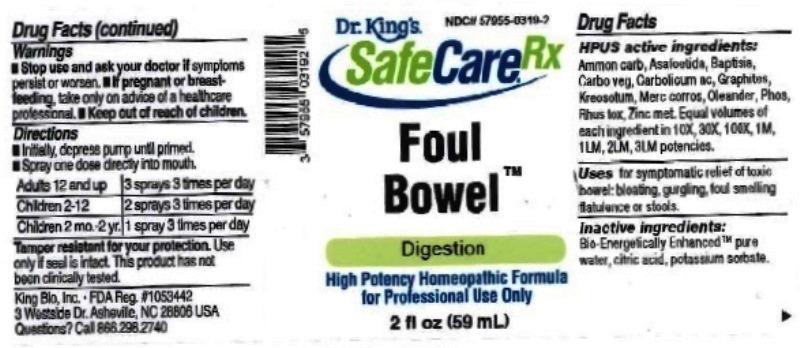 DRUG LABEL: Foul Bowel
NDC: 57955-0319 | Form: LIQUID
Manufacturer: King Bio Inc.
Category: homeopathic | Type: HUMAN OTC DRUG LABEL
Date: 20161121

ACTIVE INGREDIENTS: AMMONIUM CARBONATE 10 [hp_X]/10 mL; ASAFETIDA 10 [hp_X]/10 mL; BAPTISIA TINCTORIA ROOT 10 [hp_X]/10 mL; ACTIVATED CHARCOAL 10 [hp_X]/10 mL; PHENOL 10 [hp_X]/10 mL; GRAPHITE 10 [hp_X]/10 mL; WOOD CREOSOTE 10 [hp_X]/10 mL; MERCURIC CHLORIDE 10 [hp_X]/10 mL; NERIUM OLEANDER LEAF 10 [hp_X]/10 mL; PHOSPHORUS 10 [hp_X]/10 mL; TOXICODENDRON PUBESCENS LEAF 10 [hp_X]/10 mL; ZINC 10 [hp_X]/10 mL
INACTIVE INGREDIENTS: ANHYDROUS CITRIC ACID; POTASSIUM SORBATE; WATER

Foul Bowel™

ACTIVE INGREDIENT

Drug Facts__________________________________________________________________________________________________________

HPUS active ingredients: Ammonium carbonicum, Asafoetida, Baptisia tinctoria, Carbo vegetabilis, Carbolicum acidum, Graphites, Kreosotum, Mercurius corrosivus, Oleander, Phosphorus, Rhus toxicodendron, Zincum metallicum. Equal volumes of each ingredient in 10X, 30X, 100X, 1M, 1LM, 2LM, 3LM potencies.

INDICATIONS AND USAGE

Uses for symptomatic relief of toxic bowel: bloating, gurgling, foul smelling flatulence or stools.

Inactive Ingredients:

Bio-Energetically Enhanced™ pure water, citric acid and potassium sorbate.

Warnings

- Stop use and ask your doctor if symptoms persist or worsen.
- If pregnant or breast-feeding, take only on advice of a healthcare professional.

- Keep out of reach of children.

Directions

- Initially, depress pump until primed.
- Spray one dose directly into mouth.
- Adults 12 and up: 3 sprays 3 times per day.
- Children 2-12: 2 sprays 3 times per day.
- Children 2 mo-2 yr: 1 spray 3 times per day.

OTHER SAFETY INFORMATION

Tamper resistant for your protection. Use only if safety seal is intact. This product has not been clinically tested.

PURPOSE

Uses for symptomatic relief of toxic bowel:

- bloating
- gurgling
- foul smelling flatulence or stools